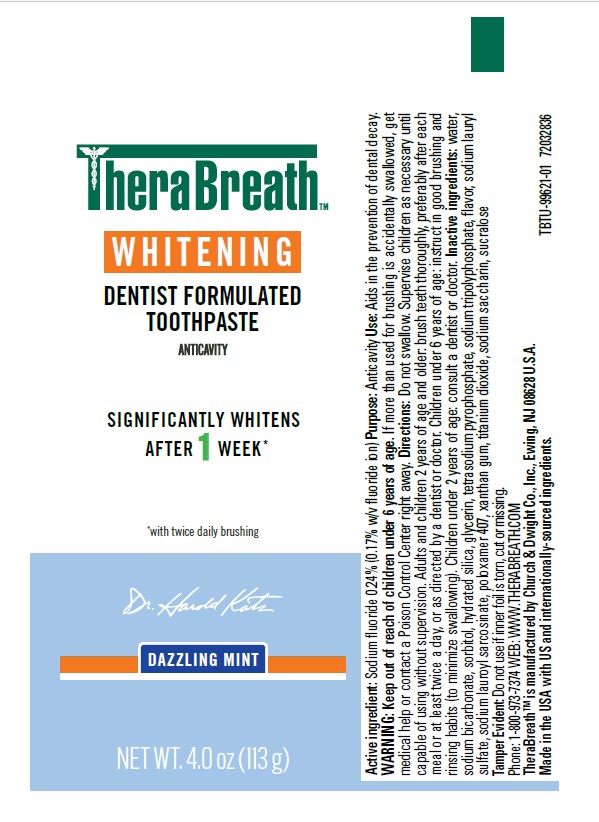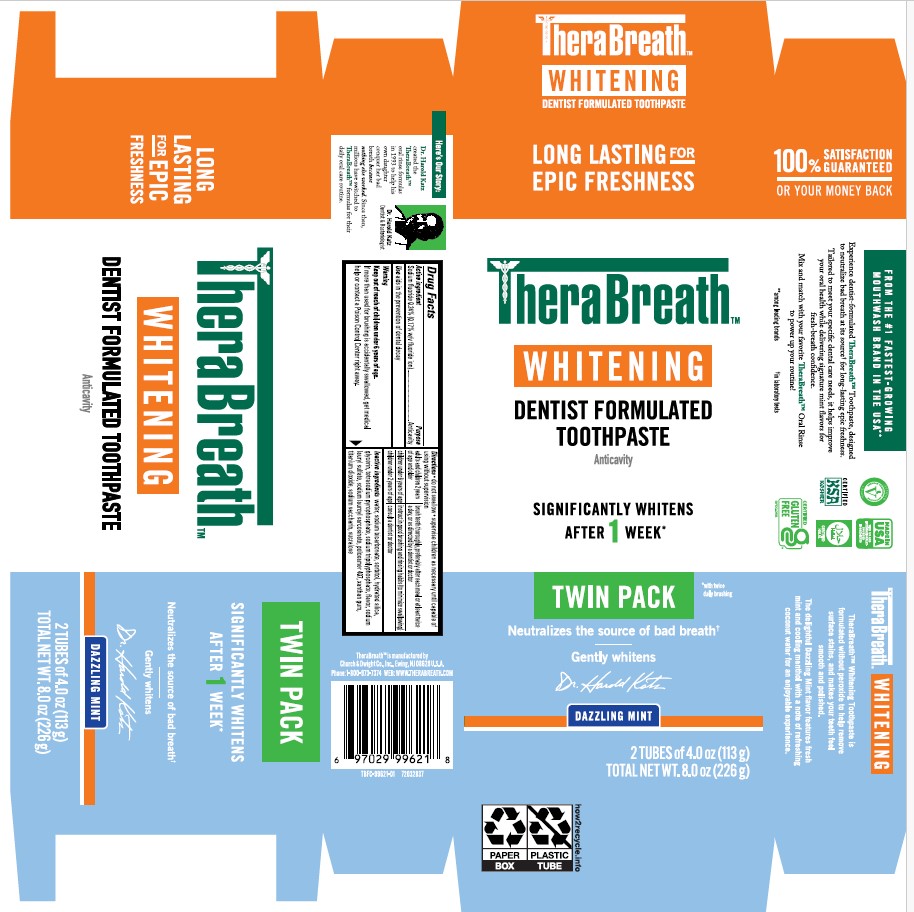 DRUG LABEL: Therabreath
NDC: 10237-272 | Form: PASTE, DENTIFRICE
Manufacturer: Church & Dwight Co., Inc.
Category: otc | Type: HUMAN OTC DRUG LABEL
Date: 20250814

ACTIVE INGREDIENTS: SODIUM FLUORIDE 0.243 g/100 g
INACTIVE INGREDIENTS: WATER; SODIUM BICARBONATE; SODIUM TRIPOLYPHOSPHATE; SODIUM LAUROYL SARCOSINATE; SUCRALOSE; TITANIUM DIOXIDE; SORBITOL; HYDRATED SILICA; SODIUM LAURYL SULFATE; POLOXAMER 407; GLYCERIN; SODIUM SACCHARIN; TETRASODIUM PYROPHOSPHATE; XANTHAN GUM

Therabreath™ Whitening Dentist Formulated Toothpaste

Drug Facts

Active Ingredient

Sodium fluoride 0.24% (0.17% w/v fluoride ion)

Purpose

Anticavity

Use

aids in the prevention of dental decay

Warning

Keep out of reach of children under 6 years of age.

If more than used for brushing is accidentally swallowed, get medical help or contact a Poison Control Center right away.

Directions

• do not swallow • supervise children as necessary until capable of using without supervision

adults and children 2 years of age and older | brush teeth thoroughly, preferably after each meal or at least twice a day, or as directed by a dentist or doctor
children under 6 years of age | instruct in good brushing and rinsing habits (to minimize swallowing)
children under 2 years of age | consult a dentist or doctor

Inactive Ingredients

water, sodium bicarbonate, sorbitol, hydrated silica, glycerin, tetrasodium pyrophosphate, sodium tripolyphosphate, flavor, sodium lauryI sulfate, sodium lauroyl sarcosinate, poloxamer 407, xanthan gum, titanium dioxide, sodium saccharin, sucralose

Questions or Comments?

TheraBreath is manufactured by

Church & Dwight Co., Inc. Ewing, NJ 08628 U.S.A.

Phone: 1-800-973-7374 WEB: WWW.THERABREATH.COM

Prinicpal Display Panel

LONG LASTING FOR EPIC FRESHNESS

TheraBreath™

WHITENING

DENTIST FORMULATED TOOTHPASTE

Anticavity

SIGNIFICANTLY WHITENS AFTER 1 WEEK*

TWIN PACK *with twice daily brushing

Neutralizes the source of bad breatht

tin laboratory tests

Gently whitens

Dr. Harold Katz

Dazzling Mint

2 TUBES of 4.0 oz (113 g)

TOTAL NET WT. 8.0 oz (226 g)